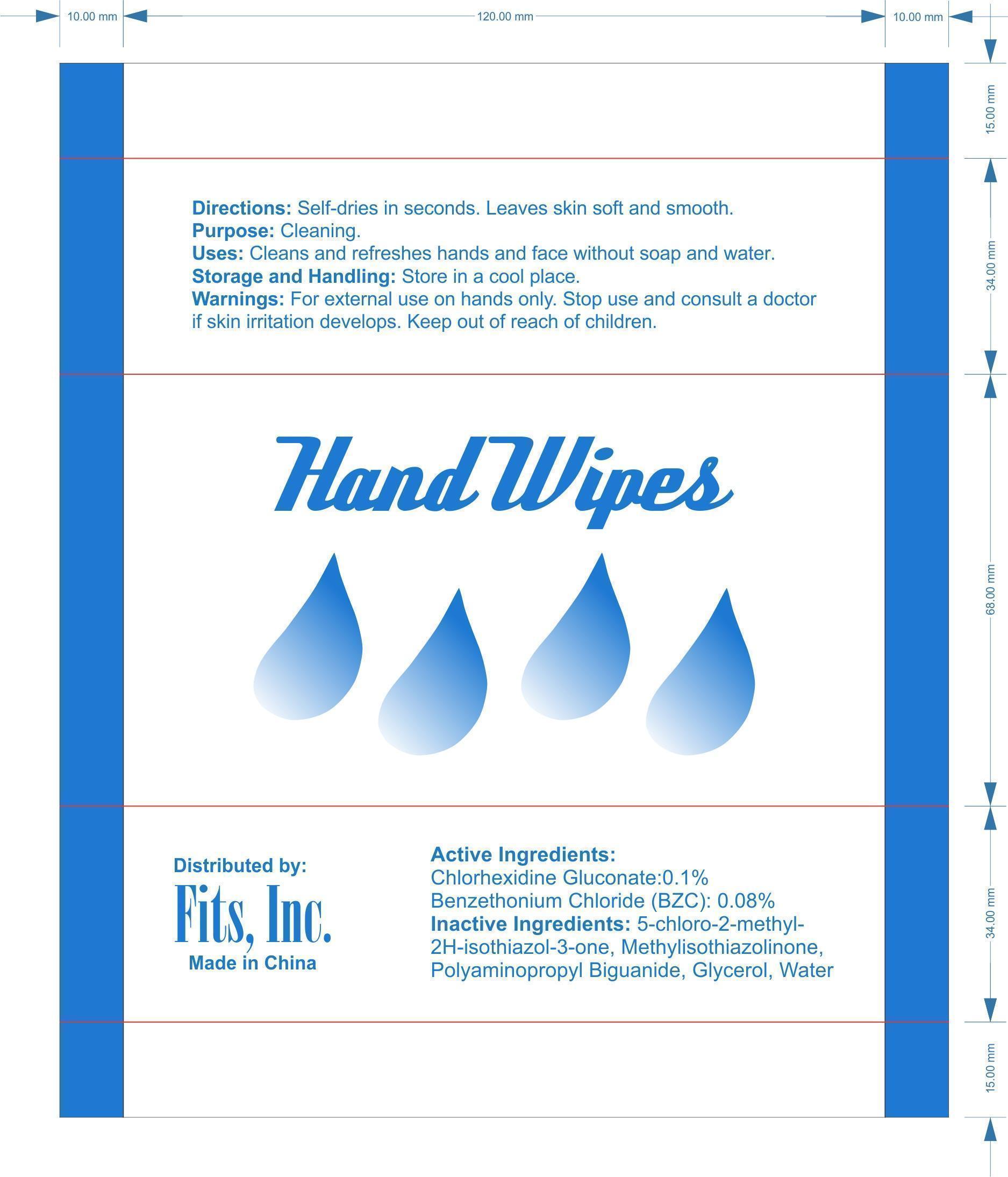 DRUG LABEL: Hand Wipes
NDC: 71734-203 | Form: CLOTH
Manufacturer: JIANGMEN SHUIZIRUN SANITARY ARTICLES CO., LTD.
Category: otc | Type: HUMAN OTC DRUG LABEL
Date: 20171009

ACTIVE INGREDIENTS: CHLORHEXIDINE GLUCONATE 0.1 g/1 g; BENZETHONIUM CHLORIDE 0.08 g/1 g
INACTIVE INGREDIENTS: GLYCERIN; POLYAMINOPROPYL BIGUANIDE; Water; Methylisothiazolinone

DRUG FACTS

Active Ingredient

Benzethonium Chloride .......... 0.08

Chlorhexidine Digluconate ........ 0.10

Purpose

Cleaning

Uses:

Cleans and refreshes hands and face without soap and water

WARNINGS

For external use only.

- for external use on hands only.
- Stop use and sonsult a doctor if skin irritation develops.
- Store in a cool place.

Keep out of reach of children.

In case of accidental ingestion, seek professional assistance or contact a Poison Control Center immediately.

Directions

Self-dries in seconds. Leaves skin soft and smooth.

Inactive Ingredients:

5-chloro-2-methyl-2H-isothiazol-3-one, Methylisothiazolinone, Polyaminopropyl Biguanide, Glycerol, Water